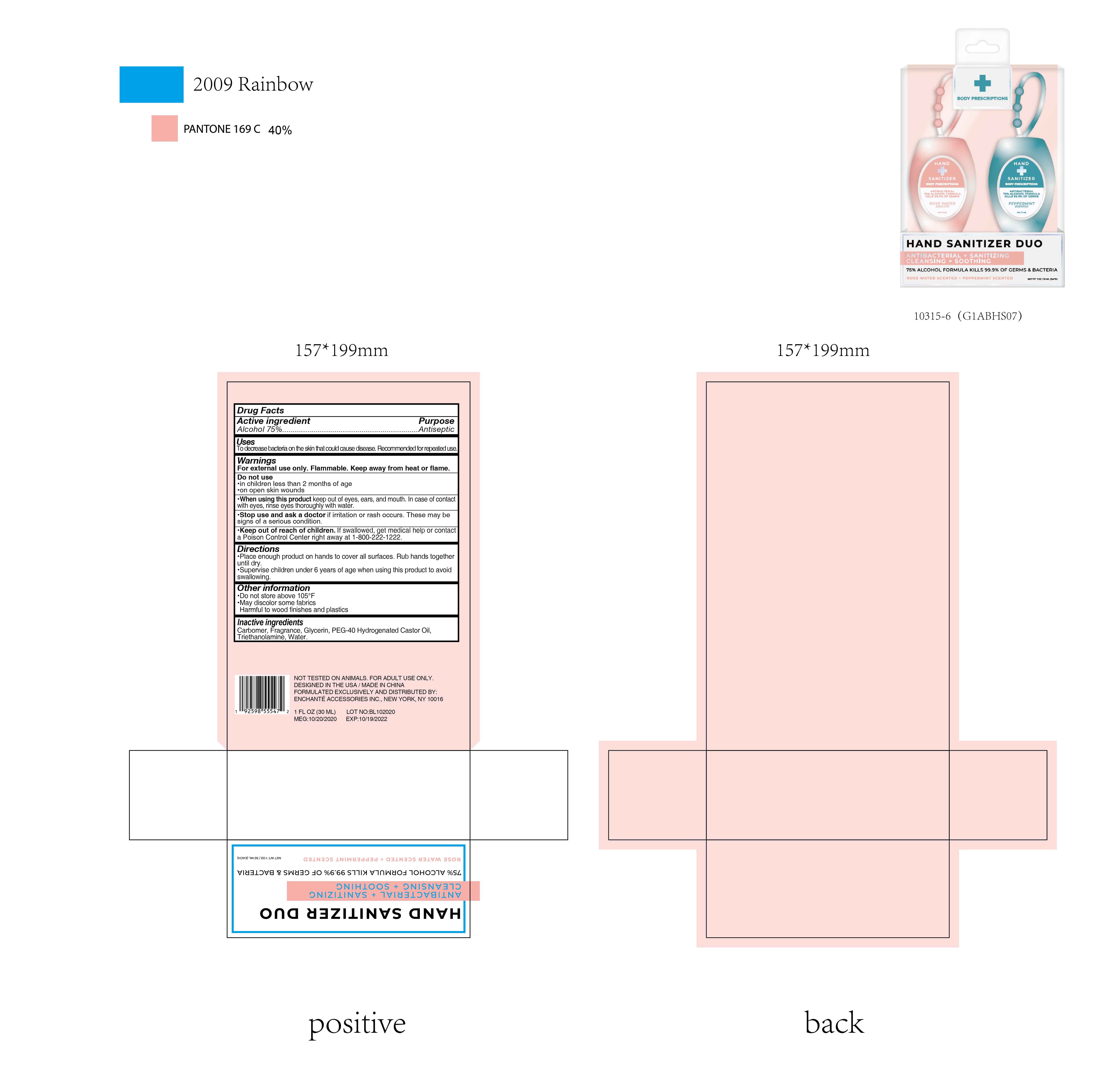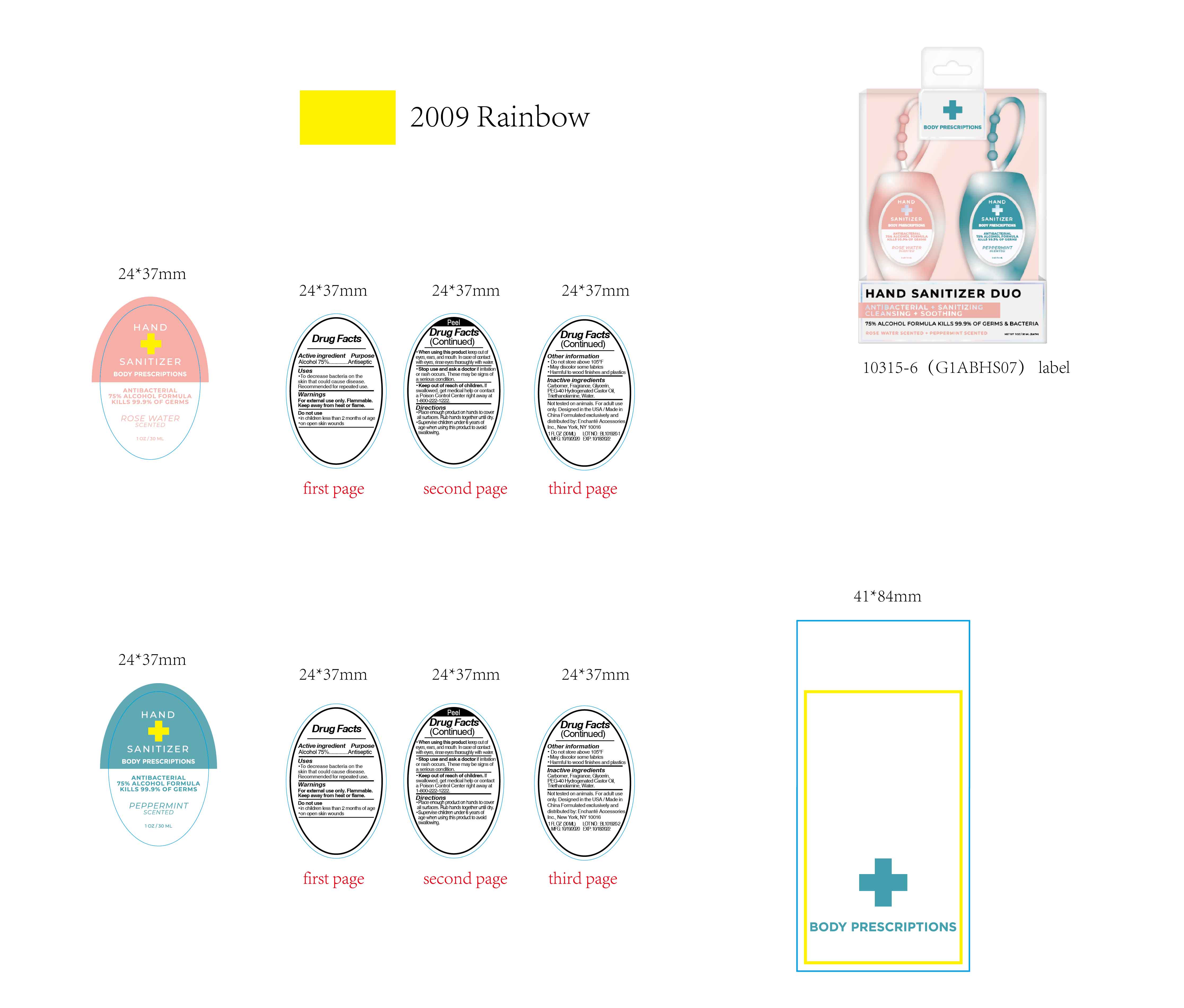 DRUG LABEL: BODY PRESCRIPTIONS HAND SANITIZER DUO ROSE WATER SCENTED PEPPERMINT SCENTED
NDC: 50563-399 | Form: KIT | Route: TOPICAL
Manufacturer: ENCHANTE ACCESSORIES INC.
Category: otc | Type: HUMAN OTC DRUG LABEL
Date: 20201101

ACTIVE INGREDIENTS: ALCOHOL 75 mL/100 mL; ALCOHOL 75 mL/100 mL
INACTIVE INGREDIENTS: WATER; GLYCERIN; CARBOMER 940; TROLAMINE; POLYOXYL 40 HYDROGENATED CASTOR OIL; WATER; GLYCERIN; CARBOMER 940; TROLAMINE; POLYOXYL 40 HYDROGENATED CASTOR OIL

50563-397/398/399 G1ABHS07

BODY PRESCRIPTIONS ANTIBACTERIAL HAND SANITIZER ROSE WATER SCENTED

Active Ingredient

Alcohol 75%

Purpose

Antiseptic

Use

■ To decrease bacteria on the skin that could cause disease
■Recommended for repeated use

WARNINGS

For external use only. Flammable.

Keep away from heat or flame

Do not use

- in children less than 2 months of age
- on open skin wounds

When using this product, keep out of eyes, ears, and mouth.
In case of contact with eyes, rinse eyes thoroughly with water

Stop use and ask a doctor if skin irritation or rash occurs. These may be signs of a serious condition

Keep out of reach of children. If swallowed, get medical help or contact a Poison Control Center right away at 1-800-222-1222

Directions

Place enough product on hands to cover all surfaces. Rub hands together until dry.

Supervise children under 6 years of age when using this product to avoid swallowing

Other information

Do not store above 105F

May discolor some fabrics

Harmful to wood finishes and plastics

Inactive ingredients

Carbomer, Fragrance, Glycerin, PEG-40 Hydrogenated Castor Oil, Triethanolamine, Water

BODY PRESCRIPTIONS ANTIBACTERIAL HAND SANITIZER PEPPERMINT SCENTED

Active Ingredient

Alcohol 75%

Purpose

Antiseptic

Uses

- To decrease bacteria on the skin that could cause disease

■Recommended for repeated use

Warnings

For external use only. Flammable.

Keep away from heat or flame

Do not use

- in children less than 2 months of age
- on open skin wounds

When using this product, keep out of eyes, ears, and mouth.
In case of contact with eyes, rinse eyes thoroughly with water

Stop use and ask a doctor if skin irritation or rash occurs. These may be a sign of serious condition

Keep out of reach of children. If swallowed, get medical help or contact a Poison Control Center right away at 1-800-222-1222

Directions

- Place enough product on hands to cover all surfaces. Rub hands together until dry.
- Supervise children under 6 years of age when using this product to avoid swallowing

Other Information

Do not store above 105F

May discolor some fabrics

Harmful to wood finishes and plastics

Inactive Ingredients

Carbomer, Fragrance, Glycerin, PEG-40 Hydrogenated Castor Oil, Triethanolamine, Water